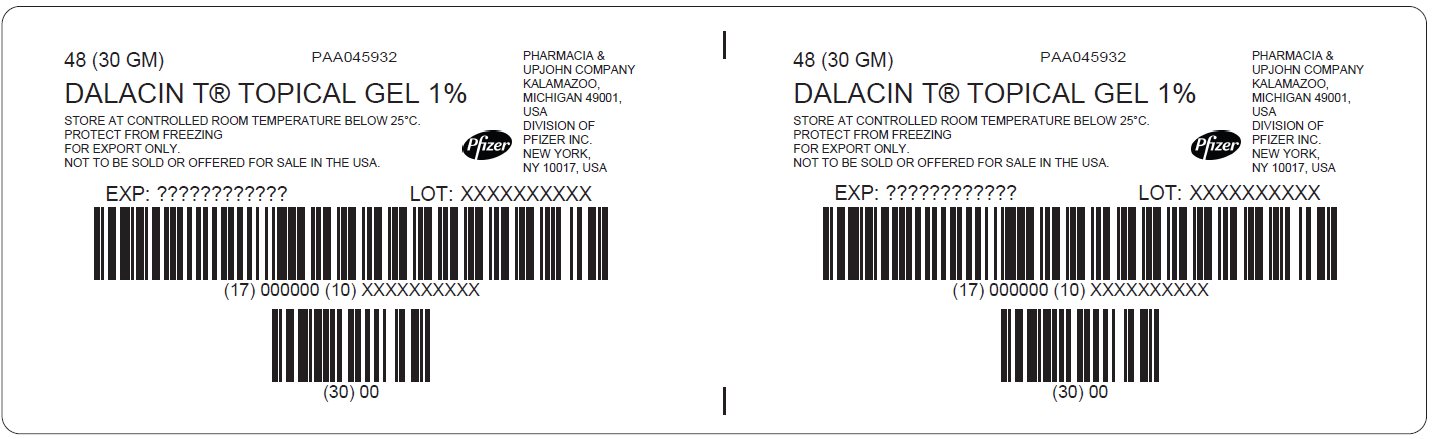 DRUG LABEL: DALACIN T
NDC: 0009-1208 | Form: GEL
Manufacturer: Pharmacia & Upjohn Company LLC
Category: prescription | Type: HUMAN PRESCRIPTION DRUG LABEL
Date: 20260210

ACTIVE INGREDIENTS: CLINDAMYCIN PHOSPHATE 10 mg/1 g
INACTIVE INGREDIENTS: CARBOMER HOMOPOLYMER TYPE B (ALLYL PENTAERYTHRITOL CROSSLINKED); ALLANTOIN; METHYLPARABEN; POLYETHYLENE GLYCOL 400; PROPYLENE GLYCOL; SODIUM HYDROXIDE; WATER

DALACIN T®

PRINCIPAL DISPLAY PANEL – Shipping Label

48 (30 GM)
PAA045932

DALACIN T® TOPICAL GEL 1%

STORE AT CONTROLLED ROOM TEMPERATURE BELOW 25°C.
PROTECT FROM FREEZING
FOR EXPORT ONLY.
NOT TO BE SOLD OR OFFERED FOR SALE IN THE USA.

PHARMACIA &
UPJOHN COMPANY
KALAMAZOO,
MICHIGAN 49001,
USA
DIVISION OF
PFIZER INC.
NEW YORK,
NY 10017, USA

Pfizer

EXP: ????????????
LOT: XXXXXXXXXX